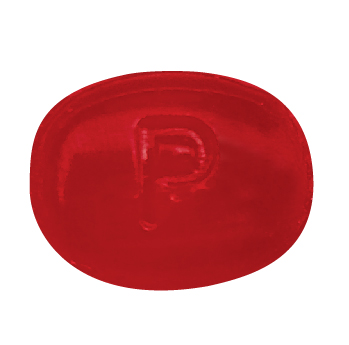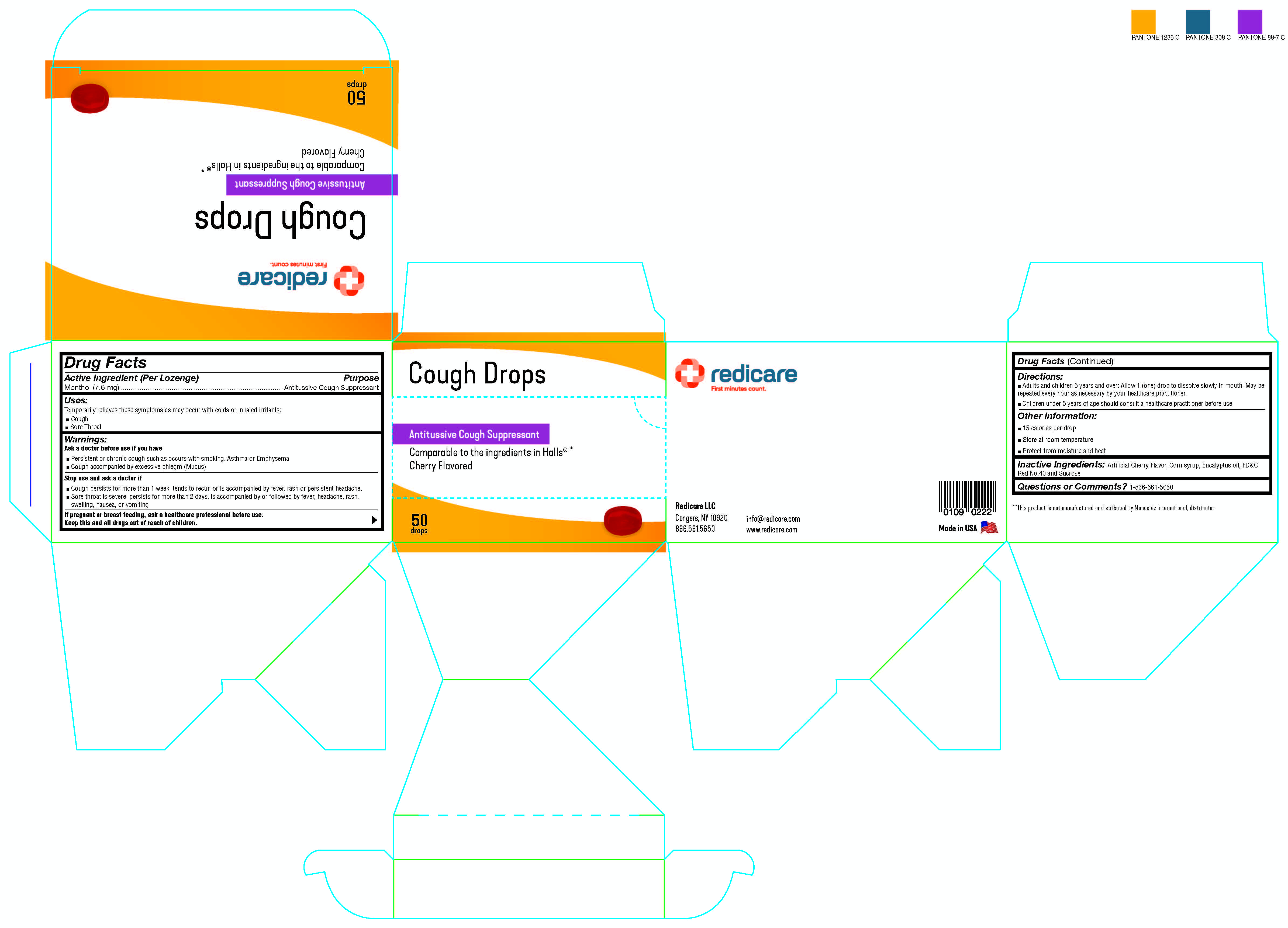 DRUG LABEL: Redicare Cough Drops Cherry Flavored
NDC: 71105-930 | Form: LOZENGE
Manufacturer: Redicare LLC
Category: otc | Type: HUMAN OTC DRUG LABEL
Date: 20250225

ACTIVE INGREDIENTS: MENTHOL, UNSPECIFIED FORM 7.6 mg/100 mg
INACTIVE INGREDIENTS: CORN SYRUP; SUCROSE; FD&C RED NO. 40; EUCALYPTUS OIL

Redicare Cherry Cough Drops

Active Ingredient (per lozenge)

Menthol (7.6 mg)

Purpose

Antitussive Cough Suppressent

Uses

Temporarily relieves these symptoms as may occur with colds or inhaled irritants:

- Cough
- Sore Throat

Warnings

Ask a doctor before use if you have

- Persistent or chronic cough such as occurs with smoking, Asthma, or Emphysema
- Cough accompanied by excessive phlegm (Mucus)

Stop use and ask a doctor if

- Cough persists for more than one week, tends to recur, or is accompanied by fever, rash, or persistent headache.
- Sore throat is severe, persists for more than two days, is accompanied by or followed by fever, headache, rash, swelling, nausea, or vomiting

Directions

Adults and children 5 years and over:

- Allow 1 (one) drop to dissolve slowly in mouth. May be repeated every hour as necessary or as directed by your healthcare practitioner.
- Children under 5 years of age should consult a healthcare practitioner before use.

Other Information

- 15 Calories Per Drop
- Store at room temperature
- Protecture from moisture and heat

Inactive ingredients

Artificial Cherry Flavor, Corn Syrup, Eucalyptus Oil, FD&C Red No. 40, and Sucrose

Questions or Comments?

1-866-561-5650